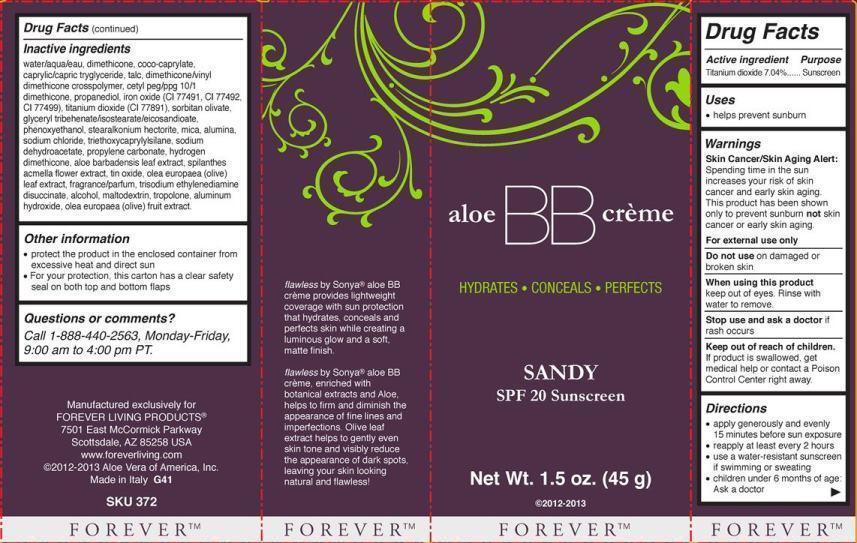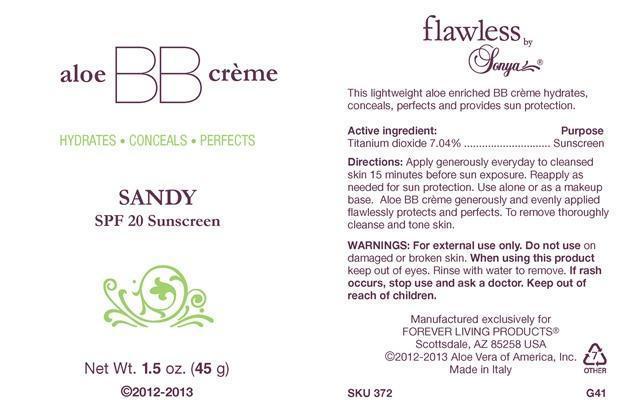 DRUG LABEL: Flawless by Sonya Aloe BB Creme
NDC: 11697-372 | Form: CREAM
Manufacturer: Aloe Vera of America, Inc.
Category: otc | Type: HUMAN OTC DRUG LABEL
Date: 20150122

ACTIVE INGREDIENTS: TITANIUM DIOXIDE 3.1680 g/45.0000 g
INACTIVE INGREDIENTS: WATER 18.8696 g/45.0000 g; DIMETHICONE 4.5923 g/45.0000 g; COCO-CAPRYLATE 2.9250 g/45.0000 g; MEDIUM-CHAIN TRIGLYCERIDES 2.8359 g/45.0000 g; TALC 1.8630 g/45.0000 g; DIMETHICONE/VINYL DIMETHICONE CROSSPOLYMER (SOFT PARTICLE) 1.7438 g/45.0000 g; CETYL PEG/PPG-10/1 DIMETHICONE (HLB 3) 1.3500 g/45.0000 g; PROPANEDIOL 1.3500 g/45.0000 g; FERRIC OXIDE RED 0.3859 g/45.0000 g; FERRIC OXIDE YELLOW 0.3859 g/45.0000 g; FERROSOFERRIC OXIDE 0.3859 g/45.0000 g; SORBITAN OLIVATE 0.9000 g/45.0000 g; GLYCERYL TRIBEHENATE/ISOSTEARATE/EICOSANDIOATE 0.9000 g/45.0000 g; PHENOXYETHANOL 0.4365 g/45.0000 g; STEARALKONIUM HECTORITE 0.3375 g/45.0000 g; MICA 0.3195 g/45.0000 g; ALUMINUM OXIDE 0.2340 g/45.0000 g; SODIUM CHLORIDE 0.2250 g/45.0000 g; TRIETHOXYCAPRYLYLSILANE 0.1620 g/45.0000 g; SODIUM DEHYDROACETATE 0.1350 g/45.0000 g; PROPYLENE CARBONATE 0.1125 g/45.0000 g; ALOE VERA LEAF 0.0450 g/45.0000 g; ACMELLA OLERACEA FLOWER 0.0441 g/45.0000 g; STANNIC OXIDE 0.0315 g/45.0000 g; OLEA EUROPAEA LEAF 0.0313 g/45.0000 g; TRISODIUM ETHYLENEDIAMINE DISUCCINATE 0.0167 g/45.0000 g; ALCOHOL 0.0135 g/45.0000 g; MALTODEXTRIN 0.0135 g/45.0000 g; TROPOLONE 0.0135 g/45.0000 g; ALUMINUM HYDROXIDE 0.0134 g/45.0000 g; BLACK OLIVE 0.0005 g/45.0000 g

Active Ingredient Purpose
Titanium dioxide 7.04%.........................Sunscreen

Uses

- helps prevent sunburn

Warnings

Skin Cancer/Skin Aging Alert: Spending time in the sun increases your risk of skin cancer and early skin aging. This product has been shown only to prevent sunburn not skin cancer or early skin aging.

For external use only

Do not use on damages or broken skin

When using this product keep out of eyes. Rinse with water to remove.

Stop use and ask a doctor if rash occurs

Keep out of reach of children. If product is swallowed, get medical help or contact a Poison Control Center right away.

Directions

- apply generously and evenly 15 minutes before sun exposure
- reapply at least every 2 hours
- use a water-resistant sunscreen if swimming or sweating
- children under 6 months of age: Ask a doctor

Inactive ingredients
water/aqua/eau, dimethicone, coco-caprylate, caprylic/capric tryglyceride, talc, dimethicone/vinyl dimethicone crosspolymer, cetyl peg/ppg 10/1 dimethicone, propanediol, iron oxide (CI 77491, CI 77492, CI 77499), titanium dioxide (CI 77891), sorbitan olivate, glyceryl tribehenate/isostearate/eicosandioate, phenoxyethanol, stearalkonium hectorite, mica, alumina, sodium chloride, triethoxycaprylylsilane, sodium dehydroacetate, propylene carbonate, hydrogen dimethicone, aloe barbadensis leaf extract, spilanthes acmella flower extract, tin oxide, olea europaea (olive) leaf extract, fragrance/parfum, trisodium ethylenediamine disuccinate, alcohol, maltodextrin, tropolone, aluminum hydroxide, olea europaea (olive) fruit extract.

Other information

- protect the product in the enclosed container from excessive heat and direct sun
- For your protection, this carton has a clear safety seal on both top and bottom flaps

Questions or comments?

Call 1-888-440-2563, Monday-Friday, 9:00 am to 4:00 pm PT.